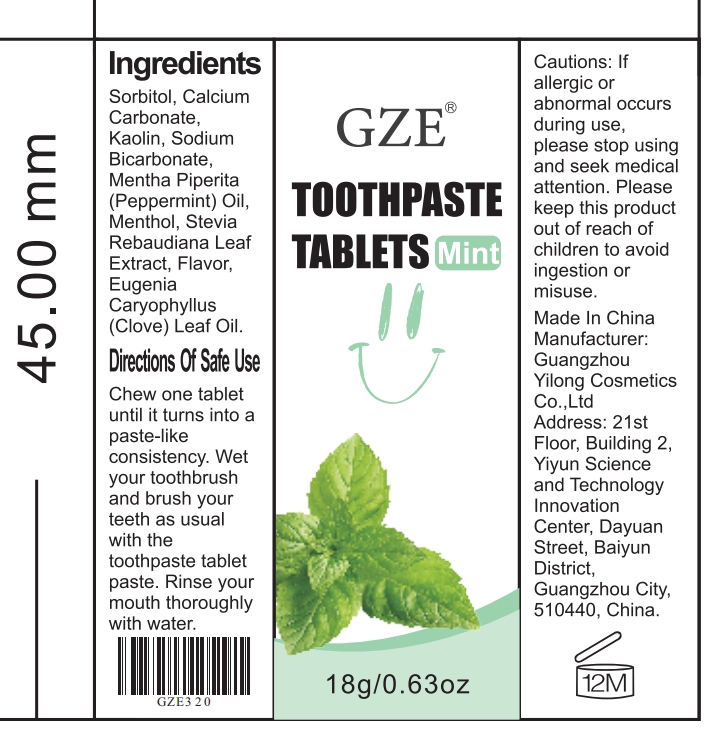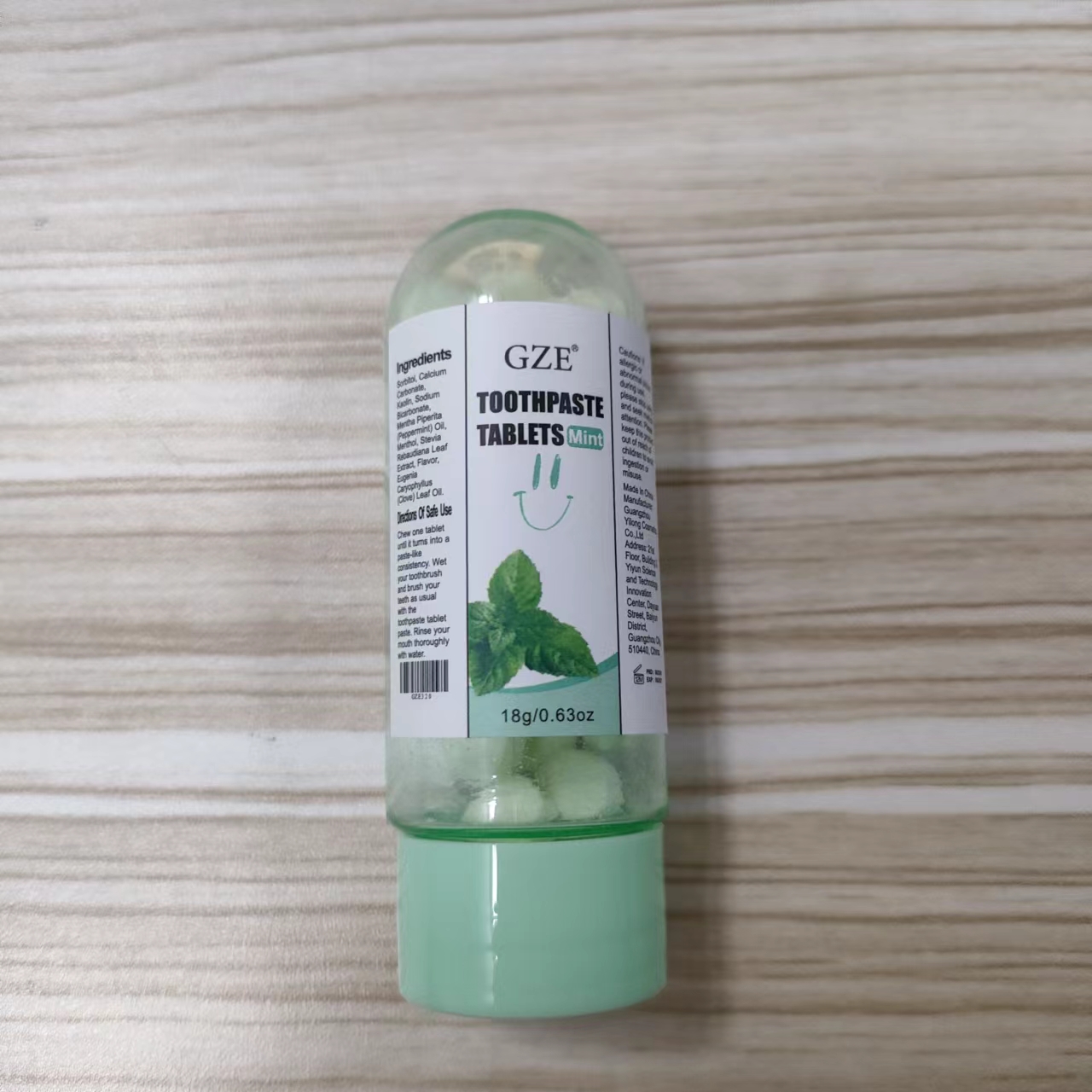 DRUG LABEL: Gze ToothpasteTablets
NDC: 83566-320 | Form: TABLET, CHEWABLE
Manufacturer: Guangzhou Yilong Cosmetics Co., Ltd
Category: otc | Type: HUMAN OTC DRUG LABEL
Date: 20240830

ACTIVE INGREDIENTS: MENTHOL 0.6 g/100 g; CLOVE OIL 5 g/100 g
INACTIVE INGREDIENTS: STEVIA REBAUDIANA LEAF; SORBITOL; CALCIUM CARBONATE; KAOLIN; SODIUM BICARBONATE; PEPPERMINT OIL

GZE TOOTHPASTE TABLETS

ACTIVE INGREDIENT

Menthol 0.6%

Eugenia Caryophyllus (Clove) Leaf Oil 5%

INACTIVE INGREDIENT

Sorbitol

Calcium Carbonate

Kaolin

Sodium Bicarbonate

Mentha Piperita (Peppermint) Oil

Stevia Rebaudiana Leaf Extract

Flavor

PURPOSE

Oral cleaning

INDICATIONS AND USAGE

Chew one tablet until it turns into a paste-like consistency. Wet your toothbrush and brush your teeth as usual with the toothpaste tablet paste. Rinse your mouth thoroughly with water.

WARNINGS

For external use only.

Stop use and ask a doctor if rash occurs.

Do not use on damaged or broken skin.

When using this product keep out of eyes. Rinse with water to remove.

Keep out of reach of children. If swallowed, get medical help or contact a Poison Control Center right away.

DOSAGE AND ADMINISTRATION

Chew one tablet until it turns into a paste-like consistency. Wet your toothbrush and brush your teeth as usual with the toothpaste tablet paste. Rinse your mouth thoroughly with water.